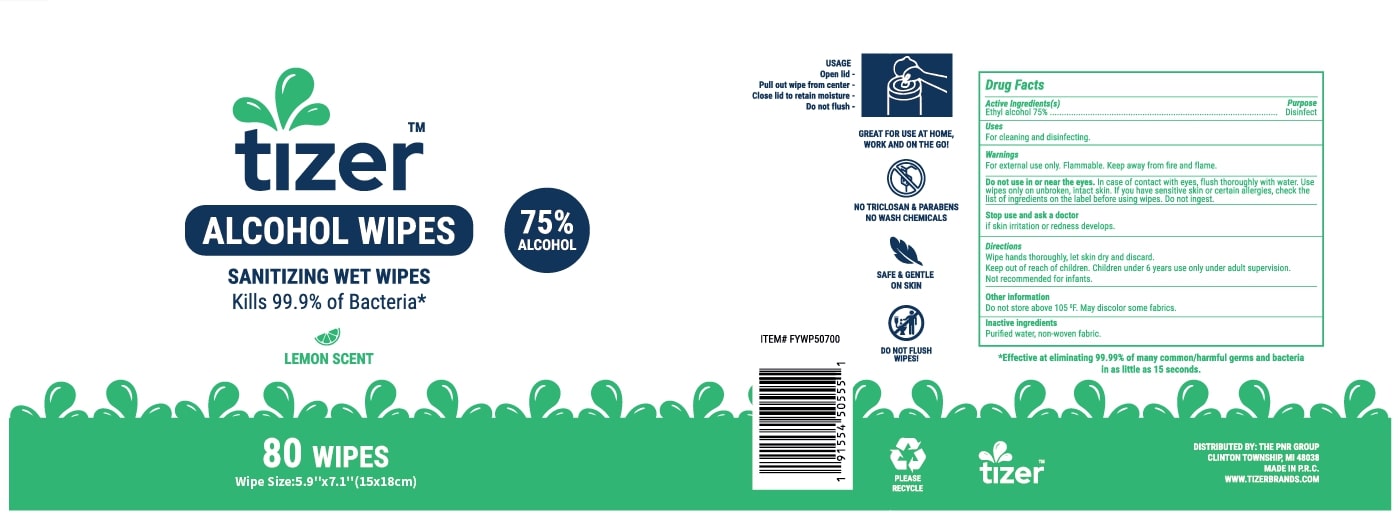 DRUG LABEL: Tizer Wipes
NDC: 80628-101 | Form: LIQUID
Manufacturer: The PnR Group, LLC
Category: otc | Type: HUMAN OTC DRUG LABEL
Date: 20200922

ACTIVE INGREDIENTS: ALCOHOL 75 mL/100 mL
INACTIVE INGREDIENTS: WATER

Tizer Wipes

Active Ingredient(s)

Alcohol 75% v/v.

Purpose

Disinfect

Use

For cleaning and disinfecting.

Warnings

For external use only. Flammable. Keep away from fire or flame

Do not use

In case of contact with eyes, flush, thoroughly with water. Use wipes only on unbroken, intact skin. If you have sensitive skin, check the list of ingredients on the label before using wipes. Do not ingest.

Stop use and ask a doctor if irritation or redness develops.

Keep out of reach of children. Children under 6 years only under adult supervision.

Directions

- Wipe hands thoroughly, let skin dry and discard.
- Not recommend for infants.

Other information

- Do not store above 105F. May discolor some fabrics.

Inactive ingredients

Purified water, non-woven fabric.